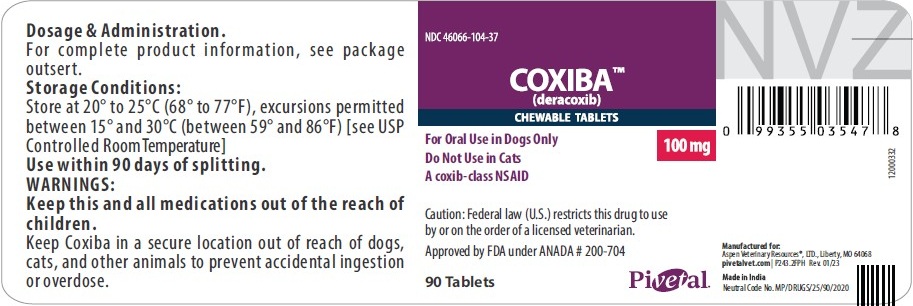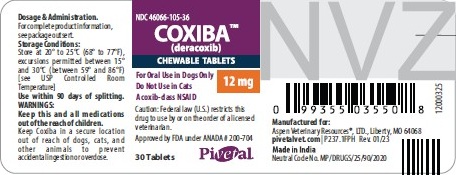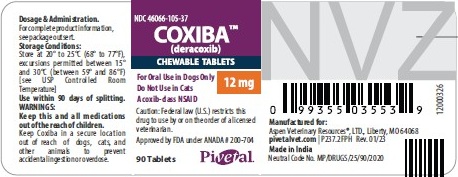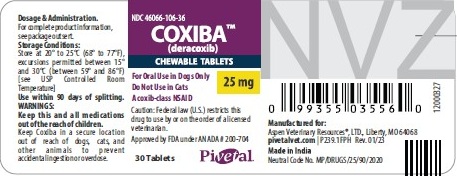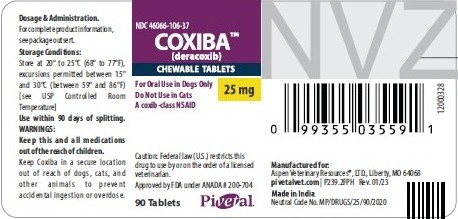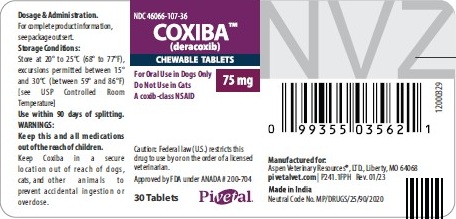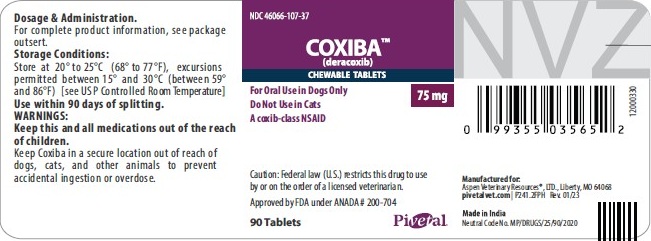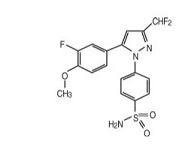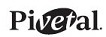 DRUG LABEL: Coxiba
NDC: 46066-105 | Form: TABLET, CHEWABLE
Manufacturer: ASPEN VETERINARY RESOURCES®, LTD
Category: animal | Type: Prescription Animal Drug Label
Date: 20260216

ACTIVE INGREDIENTS: DERACOXIB 12 mg/1 1

Coxiba™ (deracoxib)
Chewable Tablets
For Oral Use in Dogs Only
Do Not Use in Cats

Caution:

Federal Law (U.S.) restricts this drug to use by or on the order of a licensed veterinarian.

Description:

CoxibaTM (deracoxib) Chewable Tablets is a non-narcotic, non-steroidal anti-inflammatory drug (NSAID) of the coxib class. Coxiba Chewable Tablets are round, light brown colored, chewable tablets that contain deracoxib formulated with beefy flavoring. The molecular weight of deracoxib is 397.38. The empirical formula is C17-H14-F3- N3-O3-S. Deracoxib is 4-[3-(difluoromethyl)-5-(3-fluoro-4-methoxyphenyl)-1H-pyrazole- 1-yl] benzenesulfonamide, and can be termed a diaryl substituted pyrazole. The structural formula is:

Clinical Pharmacology

Mode of Action:

Coxiba Chewable Tablets are a member of the coxib class of non-narcotic, nonsteroidal, cyclooxygenase-inhibiting anti-inflammatory drugs for the control of postoperative pain and inflammation associated with orthopedic and dental surgery and for the control of pain and inflammation associated with osteoarthritis in dogs.

Data indicate that deracoxib inhibits the production of PGE1 and 6-keto PGF1 by its inhibitory effects on prostaglandin biosynthesis.^1 Deracoxib inhibited COX-2 mediated PGE2 production in LPS-stimulated human whole blood.^2

Cyclooxygenase-1 (COX-1) is the enzyme responsible for facilitating constitutive physiological processes (e.g., platelet aggregation, gastric mucosal protection, renal perfusion).^3 Cyclooxygenase-2 (COX-2) is responsible for the synthesis of inflammatory mediators.^4 Both COX isoforms are constitutively expressed in the canine kidney.^5 At doses of 2-4 mg/kg/day, deracoxib tablets do not inhibit COX-1 based on in vitro studies using cloned canine cyclooxygenase.^6 The clinical relevance of this in vitro data has not been shown.

Although the plasma terminal elimination half-life for deracoxib tablets is approximately 3 hours, a longer duration of clinical effectiveness is observed.

Summary pharmacokinetics of deracoxib tablets are listed in Table 1.

Table 1: Pharmacokinetics of Deracoxib
Parameter | Value
Tmaxa | 2 hours
Oral Bioavailability (F)a | > 90% at 2 mg/kg
Terminal elimination half-lifeb | 3 hours at 2-3 mg/kg 19 hours at 20 mg/kg
Systemic Clearanceb | ~ 5 ml/kg/min at 2 mg/kg ~ 1.7 ml/kg/min at 20 mg/kg
Volume of Distributionc | ~ 1.5 L/kg
Protein bindingd | > 90%

aValues obtained following a single 2.35 mg/kg dose

bEstimates following IV administration of deracoxib as an aqueous solution
cBased upon a dose of 2 mg/kg of deracoxib
d Based upon in vitro plasma concentrations of 0.1, 0.3, 1.0, 3.0, 10.0 μg/ml

Non-linear elimination kinetics are exhibited at doses above 8 mg/kg/day, at which competitive inhibition of constitutive COX-1 may occur.

Deracoxib is not excreted as parent drug in the urine. The major route of elimination of deracoxib is by hepatic biotransformation producing four major metabolites, two of which are characterized as products of oxidation and o-demethylation. The majority of deracoxib is excreted in feces as parent drug or metabolite.
Large intersubject variability was observed in drug metabolite profiles of urine and feces. No statistically significant differences between genders were observed.

Indications and Usage:

Always provide “Information for Dog Owners” Sheet with prescription. Carefully consider the potential benefits and risk of Coxiba Chewable Tablets and other treatment options before deciding to use Coxiba Chewable Tablets. Use the lowest effective dose for the shortest duration consistent with individual response.

Osteoarthritis Pain and Inflammation:

Coxiba Chewable Tablets are indicated for the control of pain and inflammation associated with osteoarthritis in dogs.

Dosage and Administration

Osteoarthritis Pain and Inflammation: 0.45 – 0.91 mg/lb/day (1 to 2 mg/kg/ day) as a single daily dose, as needed. Dogs needing a dose of less than 12.5 mg can only be accurately dosed through use of the 12 mg tablet, which can be broken in half to provide 6 mg. Do not attempt to accurately dose smaller dogs through the use of breaking larger tablets. Inaccurate dosing may result in adverse drug events (see Adverse Reactions, Animal Safety, and Post-Approval Experience).

Postoperative Orthopedic Pain and Inflammation:

Coxiba Chewable Tablets are indicated for the control of postoperative pain and inflammation associated with orthopedic surgery in dogs.

Dosage and Administration

Postoperative Orthopedic Pain and Inflammation: 1.4 – 1.8 mg/lb/day (3 to 4 mg/kg/day) as a single daily dose, as needed, not to exceed 7 days of administration.

Dogs needing a dose of less than 12.5 mg can only be accurately dosed through use of the 12 mg tablet, which can be broken in half to provide 6 mg. Do not attempt to accurately dose smaller dogs through the use of breaking larger tablets. Inaccurate dosing may result in adverse drug events (see Adverse Reactions, Animal Safety, and Post-Approval Experience).

Postoperative Dental Pain and Inflammation:

Coxiba Chewable Tablets are indicated for the control of postoperative pain and inflammation associated with dental surgery in dogs.

Dosage and Administration

Postoperative Dental Pain and Inflammation: 0.45 – 0.91 mg/lb/day (1 to 2 mg/kg/day) as a single daily dose, for 3 days. The first dose should be given approximately 1 hour prior to dental surgery and subsequent doses should be given daily for up to two additional treatments.

Dogs needing a dose of less than 12.5 mg can only be accurately dosed through use of the 12 mg tablet, which can be broken in half to provide 6 mg. Do not attempt to accurately dose smaller dogs through the use of breaking larger tablets. Inaccurate dosing may result in adverse drug events (see Adverse Reactions, Animal Safety, and Post-Approval Experience).

Since deracoxib tablet bioavailability is greatest when taken with food, postprandial administration is preferable. However, deracoxib tablets have been shown to be effective under both fed and fasted conditions; therefore, they may be administered in the fasted state if necessary. For postoperative orthopedic and dental pain, administer Coxiba Chewable Tablets prior to the procedure. Tablets are scored and dosage should be calculated in half-tablet increments. In clinical practice it is recommended to adjust the individual patient dose while continuing to monitor the dog's status until a minimum effective dose has been reached.

Contraindications:

Dogs with known hypersensitivity to deracoxib should not receive Coxiba Chewable Tablets.

Warnings:

Not for use in humans. Keep this and all medications out of reach of children. Consult a physician in case of accidental ingestion by humans. For use in dogs only. Do not use in cats.

Dogs needing a dose of less than 12.5 mg can only be accurately dosed through use of the 12 mg tablet, which can be broken in half to provide 6 mg. Do not attempt to accurately dose smaller dogs through the use of breaking larger tablets. Inaccurate dosing may result in adverse drug events (see Adverse Reactions, Animal Safety, and Post-Approval Experience).

All dogs should undergo a thorough history and physical examination before the initiation of NSAID therapy. Appropriate laboratory tests to establish hematological and serum biochemical baseline data prior to, and periodically during, administration of any NSAID is recommended. Owners should be advised to observe for signs of potential drug toxicity (see Adverse Reactions, Animal Safety and Post-Approval Experience) and be given an “Information for Dog Owners” Sheet.

Keep Coxiba in a secure location out of reach of dogs, cats, and other animals to prevent accidental ingestion or overdose.

Precautions:

Dogs needing a dose of less than 12.5 mg can only be accurately dosed through use of the 12 mg tablet, which can be broken in half to provide 6 mg. Do not attempt to accurately dose smaller dogs through the use of breaking larger tablets. Inaccurate dosing may result in adverse drug events (see Adverse Reactions, Animal Safety, and Post-Approval Experience).

Since NSAIDs possess the potential to produce gastrointestinal ulceration and/or perforation, concomitant use of Coxiba Chewable Tablets with other anti-inflammatory drugs, such as NSAIDs or corticosteroids, should be avoided. As a class, NSAIDs may be associated with gastrointestinal, renal and hepatic toxicity. The following collective group of clinical signs has been reported with some serious gastrointestinal events, in decreasing order of reported frequency: anorexia, tachycardia, tachypnea, pyrexia, ascites, pale mucous membranes, dyspnea. In some cases, circulatory shock, collapse and cardiac arrest have also been reported. Sensitivity to drug-associated adverse events varies with the individual patient. Dogs that have experienced adverse reactions from one NSAID may experience adverse reactions from another NSAID.
Patients at greatest risk for adverse events are those that are dehydrated, on concomitant diuretic therapy, or those with existing renal, cardiovascular, and/ or hepatic dysfunction. Plasma levels of deracoxib may increase in a greater than dose- proportional fashion above 8 mg/kg/day. Deracoxib tablets have been safely used during field studies in conjunction with other common medications, including heartworm preventatives, anthelmintics, anesthetics, pre-anesthetic medications, and antibiotics. If additional pain medication is needed after a daily dose of Coxiba Chewable Tablets, a non- NSAID/non-corticosteroid class of analgesic may be necessary. It is not known whether dogs with a history of hypersensitivity to sulfonamide drugs will exhibit hypersensitivity to Coxiba Chewable Tablets. The safe use of deracoxib tablets in dogs younger than 4 months of age, dogs used for breeding, or in pregnant or lactating dogs has not been evaluated.
NSAIDs may inhibit the prostaglandins which maintain normal homeostatic function. Such anti-prostaglandin effects may result in clinically significant disease in patients with underlying or pre-existing disease that has not been previously diagnosed. Appropriate monitoring procedures should be employed during all surgical procedures. The use of parenteral fluids during surgery should be considered to decrease potential renal complications when using NSAIDs perioperatively. Concurrent administration of potentially nephrotoxic drugs should be carefully approached.
The use of concomitantly protein-bound drugs with deracoxib tablets has not been studied in dogs. Commonly used protein-bound drugs include cardiac, anticonvulsant and behavioral medications. The influence of concomitant drugs that may inhibit metabolism of deracoxib tablets has not been evaluated. Drug compatibility should be monitored in patients requiring adjunctive therapy. Consider appropriate washout times when switching from one NSAID to another or when switching from corticosteroid use to NSAID use.

Animal Safety:

In a 6-month study, dogs were dosed with deracoxib at 0, 2, 4, 6, 8 and 10 mg/kg with food once daily for 6 consecutive months. There were no abnormal feces, and no abnormal findings on clinical observations, food and water consumption, body weights, physical examinations, ophthalmoscopic evaluations, macroscopic pathological examinations, hematology, or buccal bleeding time. Urinalysis results showed hyposthenuria (specific gravity <1.005) and polyuria in one male and one female in the 6 mg/kg group after 6 months of treatment. After 6 months of treatment, the mean BUN values for dogs treated with 6, 8, or 10 mg/kg/day were 30.0, 35.3, and 48.2 mg/dL respectively. No effects were seen on any other clinical chemistry parameters, including other variables associated with renal physiology (serum creatinine, serum electrolytes, and urine sediment evaluation). Dose dependent focal renal tubular degeneration/regeneration was seen in some dogs treated at 6, 8, and 10 mg/kg/day. Focal renal papillary necrosis was seen in 3 dogs dosed at 10 mg/kg/day and in one dog dosed at 8 mg/kg/day. No renal lesions were seen at the label doses of 2 and 4 mg/kg/day. There was no evidence of gastrointestinal, hepatic, or hematopoietic pathology at any of the doses tested.

In a laboratory study, healthy young dogs were dosed with deracoxib tablets once daily, within 30 minutes of feeding, at doses of 0, 4, 6, 8, and 10 mg/kg body weight for 21 consecutive days. No adverse drug events were reported. There were no abnormal findings reported for clinical observations, food and water consumption, body weights, physical examinations, ophthalmic evaluations, organ weights, macroscopic pathologic evaluation, hematology, urinalyses, or buccal mucosal bleeding time. In the clinical chemistry results there was a statistically significant (p<0.0009) dose-dependent trend toward increased levels of blood urea nitrogen (BUN). Mean BUN values remained within historical normal limits at the label dose. No effects on other clinical chemistry values associated with renal function were reported. There was no evidence of renal, gastrointestinal, hepatic or biliary lesions noted during gross necropsy. Renal histopathology revealed trace amounts of tubular degeneration/regeneration in all dose groups including placebo, but no clear dose relationship could be determined. There was no histopathologic evidence of gastrointestinal, hepatic or biliary lesions.

In another study, micronized deracoxib in gelatin capsules was administered once daily to healthy young dogs at doses of 10,25, 50, and 100 mg/kg body weight for periods up to 14 consecutive days. Food was withheld prior to dosing. Non-linear elimination kinetics occurred at all doses. At doses of 25, 50, and 100 mg/kg, reduced body weight, vomiting, and melena occurred. Necropsy revealed gross gastrointestinal lesions in dogs from all dose groups. The frequency and severity of the lesions increased with escalating doses. At 10 mg/kg, moderate diffuse congestion of gut associated lymphoid tissues (GALT) and erosions/ulcers in the jejunum occurred. At 100 mg/kg, all dogs exhibited gastric ulcers and erosions/ulcerations of the small intestines. There were no hepatic or renal lesions reported at any dose in this study.

In a 13-week study, deracoxib in gelatin capsules was administered to healthy dogs at doses of 0, 2, 4, and 8 mg/kg/day. No test-article related changes were identified in clinical observations, physical exams, or any of the other parameters measured. One dog in the 8 mg/kg dose group died from bacterial septicemia secondary to a renal abscess. The relationship between deracoxib administration and the renal abscess is not clear.

Effectiveness:

Deracoxib tablets were evaluated in masked, placebo-controlled multi-site field studies involving client-owned animals to determine effectiveness.

Osteoarthritis Pain and Inflammation Field Study:

Two hundred and nine (209) client-owned dogs with clinical and radiographic signs of osteoarthritis of at least one appendicular joint were enrolled in this study. A total of 194 dogs were included in the safety evaluation and a total of 181 dogs were included in the effectiveness evaluation. The effectiveness of deracoxib tablets in the control of pain and inflammation associated with osteoarthritis was demonstrated in a placebo-controlled, masked study evaluating the anti-inflammatory and analgesic effects of deracoxib tablets. Tablets were administered by the owner at approximately 1-2 mg/kg/day for forty-three (43) consecutive days.
In general, statistically significant (p≤ 0.05) differences in favor of deracoxib were seen for force plate parameters (vertical impulse area, peak vertical force) and owner evaluations (quality of life, lameness and overall level of activity).
The results of this field study demonstrate that deracoxib tablets, when administered at 1-2 mg/kg/day for 43 days, are effective for the control of pain and inflammation associated with osteoarthritis.

Adverse Reactions:

Deracoxib was well tolerated and the incidence of clinical adverse reactions was comparable in deracoxib and placebo-treated animals. A total of 209 dogs of 41 breeds, 1-14 years old, weighing 17-177 lbs were included in the field safety analysis. The following table shows the number of dogs displaying each adverse reaction.

Abnormal Health Findings in the Osteoarthritis Field Study^1

Clinical Observation | Deracoxib tablets N= 105 | Placebo N = 104
Vomiting | 3 | 4
Diarrhea/soft stool | 3 | 2
Weight loss | 1 | 0
Abdominal pain (splinting) | 0 | 1
Seizure | 1 | 0
Lethargy | 0 | 1
Pyoderma/Dermatitis | 2 | 0
Unilateral conjuctivitis | 1 | 0
Scleral injection | 0 | 1
Hematuria/UTI | 1 | 0
Splenomegaly* | 1 | 0
Grade II murmur systolic | 1 | 0

^1Dogs may have experienced more than one adverse reaction during the study.
* This dog was less active and eating less on enrollment, with elevated WBC, amylase, and AST and died 1 month after exiting the study. The dog was withdrawn from the study on Day 17 with anorexia, lethargy and a suspicion of diarrhea. Follow-up laboratory analyses revealed hypoalbuminemia, hyperphosphatemia, elevated AST and decreased BUN. Follow-up treatment included other anti-inflammatories and antibiotics.
Complete blood count, serum chemistry, and buccal bleeding time analysis were conducted at the beginning and end of the trial. Mean values of all CBC and chemistry results for both deracoxib and placebo-treated dogs were within normal limits.
There was no statistically significant difference in the buccal bleeding time between deracoxib and placebo-treated dogs before or after the study, and all results remained within normal limits (less than 5 minutes). The results of this field study demonstrate that deracoxib is safe and effective for the control of pain and inflammation associated with osteoarthritis in dogs.
During this trial, dogs were safely treated with a variety of commonly used medications, including antibiotics, anti-parasiticides, topical flea adulticides and thyroid supplements.
The results of this field study demonstrate that deracoxib tablets are well tolerated when administered at 1-2 mg/kg/day for up to 43 days for the control of pain and inflammation associated with osteoarthritis.

Postoperative Orthopedic Pain and Inflammation Field Study:

In this study, 207 dogs admitted to veterinary hospitals for repair of a cranial cruciate injury were randomly administered deracoxib tablets or a placebo. Drug administration started the evening before surgery and continued once daily for 6 days postoperatively. Effectiveness was evaluated in 119 dogs and safety was evaluated in 207 dogs. Statistically significant differences in favor of deracoxib tablets were found for lameness at walk and trot, and pain on palpation values at all post-surgical time points. The results of this field study demonstrate that deracoxib tablets, when administered daily for 7 days are effective for the control of postoperative pain and inflammation associated with orthopedic surgery.

Adverse Reactions:

A total of 207 dogs of forty-three (43) different breeds, 1-15 years old, weighing 7-141 lbs were included in the field safety analysis. The following table shows the number of dogs displaying each adverse reaction.

Abnormal Health Findings in The Postoperative Orthopedic Pain Field Study^1

Clinical Observation | Deracoxib tablets N = 105 | Placebo N = 102
Vomiting | 11 | 6
Diarrhea | 6 | 7
Hematochezia | 4 | 0
Melena | 0 | 1
Anorexia | 0 | 4
Incision site lesion (drainage, oozing) | 11 | 6
Non-incision skin lesions (moist dermatitis, pyoderma) | 2 | 0
Otitis externa | 2 | 0
Positive joint culture | 1 | 0
Phlebitis | 1 | 0
Hematuria | 2 | 0
Conjunctivitis | 1 | 2
Splenomegaly | 1 | 0
Hepatomegaly | 1 | 0
Death | 0 | 1

^1 Dog may have experienced more than one adverse reaction during the study.

This table does not include one dog that was dosed at 16.92 mg/kg/day for the study duration. Beginning on the last day of treatment, this dog experienced vomiting, diarrhea, increased water intake and decreased appetite. Hematology and clinical chemistry values were unremarkable. The dog recovered uneventfully within 3 days of cessation of dosing.

Incisional drainage was most prevalent in dogs enrolled at a single study site. There were no statistically significant changes in the mean values for hepatic or renal clinical pathology indices between deracoxib tablet and placebo treated dogs. Four deracoxib tablet-treated dogs and two placebo-treated dogs exhibited elevated bilirubin during the dosing phase. One deracoxib tablet-treated dog exhibited elevated ALT, BUN and total bilirubin and a single vomiting event. None of the changes in clinical pathology values were considered clinically significant.

The results of this clinical study demonstrate that deracoxib tablets, when administered daily for 7 days to control postoperative orthopedic pain and inflammation in dogs, are well tolerated.

Postoperative Dental Pain and Inflammation Field Study:

In this study, 62 dogs admitted to veterinary hospitals for dental extractions were randomly administered deracoxib tablets or a placebo. Drug administration started approximately 1 hour before surgery and continued once daily for 2 days postoperatively. Effectiveness was evaluated in 57 dogs and safety was evaluated in 62 dogs. There was a statistically significant reduction (p=0.0338) in the proportion of dogs that required rescue therapy to control post-surgical pain in the deracoxib treated group compared to the placebo control group. Pain assessors used a modification of the Glasgow Composite Pain Scale (mGCPS) to assess pain.^7 A dog was rescued if it scored ≥ 4 on the combined mGCPS variables of Posture/Activity, Demeanor, Response to Touch, and Vocalization, or if the investigator determined at any time that pain intervention was needed. The results of this field study demonstrate that deracoxib, when administered once daily for 3 days, is effective for the control of postoperative pain and inflammation associated with dental surgery.

Adverse Reactions:

A total of 62 male and female dogs of various breeds, 1.5-16 years old, were included in the field safety analysis. The following table shows the number of dogs displaying each adverse reaction. Digestive tract disorders (diarrhea and vomiting) and systemic disorders (abnormal clinical chemistry results) were the most frequently reported findings. There were no distinct breed, age, or sex predilections for adverse reactions that were reported. No dogs were withdrawn from the study due to the occurrence of an adverse reaction.

Abnormal Health Findings in the Dental Pain Field Study^1
Clinical Observation | Deracoxib Tablets N=31 | Placebo N=31
Vomiting | 4 | 1
Diarrhea/soft stool | 3 | 1
Regurgitation | 0 | 2
Increased AST^2 | 3 | 0
Increased ALT^2 | 1 | 0
Hematuria | 1 | 0
Leukocytosis | 1 | 1
Neutrophilia | 1 | 1
Lameness | 1 | 0
Facial swelling | 0 | 1
Tachycardia | 0 | 1

^1Dogs may have experienced more than one adverse reaction during the study.
^2Included animals with results over 2x the high normal.

Post Approval Experience (Rev. 2010):

The following adverse events are based on post-approval adverse drug experience reporting. Not all adverse reactions are reported to FDA CVM. It is not always possible to reliably estimate the adverse event frequency or establish a causal relationship to product exposure using this data. The following adverse events are grouped by body system and are presented in decreasing order of reporting frequency.

Gastrointestinal: vomiting, diarrhea, hypoalbuminemia, melena, hematochezia, elevated amylase/lipase, hematemesis, abdominal pain, peritonitis, decreased or increased total protein and globulin, gastrointestinal perforation, gastrointestinal ulceration, hypersalivation.

General: anorexia, depression/lethargy, weight loss, weakness, fever, dehydration

Hepatic: elevated liver enzymes, hyperbilirubinemia, icterus, ascites, decreased BUN

Hematologic: anemia, leukocytosis, leukocytopenia, thrombocytopenia

Neurologic: seizures, ataxia, recumbency, trembling, confusion, collapse, hind limb paresis, nystagmus, proprioceptive disorder, vestibular signs

Behavioral: nervousness, hyperactivity, aggression, apprehension

Urologic: elevated BUN/creatinine, polydipsia, polyuria, hyper-phosphatemia, hematuria, low urine specific gravity, urinary incontinence, renal failure, urinary tract infection

Dermatologic: pruritus, erythema, urticaria, moist dermatitis, facial/muzzle edema, dermal ulceration/necrosis

Respiratory: panting, dyspnea, epistaxis, coughing

Cardiovascular: tachycardia, heart murmur, bradycardia, arrest

Sensory: Vestibular signs, glazed eyes, uveitis.

Ophthalmic: blindness, mydriasis, conjunctivitis, keratoconjunctivitis sicca, uveitis.

In some cases, death has been reported as an outcome of the adverse events listed above.
To report suspected adverse drug events, for technical assistance or to obtain a copy of the Safety Data Sheet, contact manufacturer at 1-833-571-1525. For additional information about adverse drug experience reporting for animal drugs, contact FDA at 1-888-FDA-VETS or http://www.fda.gov/reportanimalae.

Chewable Tablets

Information for Dog Owners:

Coxiba Chewable Tablets, like other drugs of its class, is not free from adverse reactions. Owners should be advised of the potential for adverse reactions and be informed of the clinical signs associated with drug intolerance. Adverse reactions may include vomiting, diarrhea, decreased appetite, dark or tarry stools, increased water consumption, increased urination, anemia, yellowing of gums, skin or white of the eye due to jaundice, lethargy, incoordination, seizure, or behavioral changes.
Serious adverse reactions associated with this drug class can occur without warning and in some cases result in death (see Warnings, Post-Approval Experience and Adverse Reactions). Owners should be advised to discontinue Coxiba Chewable Tablets therapy and contact their veterinarian immediately if signs of intolerance are observed.
The vast majority of patients with drug related adverse reactions have recovered when the signs are recognized, the drug is withdrawn, and veterinary care, if appropriate, is initiated. Owners should be advised of the importance of periodic follow up for all dogs during administration of any NSAID.

Storage Conditions:

Coxiba Chewable Tablets should be Store at 20° to 25°C (68° to 77°F), excursions permitted between 15° and 30°C (between 59° and 86°F) [see USP Controlled Room Temperature]
Keep this and all medications out of reach of children.
Use within 90 days of splitting.

How Supplied:

Coxiba Chewable Tablets are available as 12 mg, 25 mg, 75 mg and 100 mg round, brownish, half-scored tablets in 30 and 90 count bottles.

NDC Number | Tablet Size | Tablets/Bottle
46066-105-36 | 12 mg | 30
46066-105-37 | 12 mg | 90
46066-106-36 | 25 mg | 30
46066-106-37 | 25 mg | 90
46066-107-36 | 75 mg | 30
46066-107-37 | 75 mg | 90
46066-104-36 | 100 mg | 30
46066-104-37 | 100 mg | 90

References:

1 Data on file under NADA 141-203
2 Data on file under NADA 141-203
3 Smith, et al.: "Pharmacological Analysis of Cyclo-oxygenase-1 in Inflammation," Proc. Natl. Acad. Sci. USA (October 1998) 95: 13313-13318, Pharmacology.
4 Zhang, et al.: "Inhibition of Cyclo-oxygenase-2 Rapidly Reverses Inflammatory Hyperalgesia and Prostaglandin E2 Production,"JPET, (1997) 283: 1069-1075.
5 Verburg, KM et al. "Cox-2 Specific Inhibitors: Definition of a New Therapeutic Concept." Amer J of Therapeutics 8, 49-64, 2001.
6 Data on file under NADA 141-203
7 Holton, L., Reid, J., Scott, E.M., Pawson, P. and Nolan, A. (2001). Development of a behaviour-based scale to measure acute pain in dogs. Veterinary Record, 148, 525-53.

Approved by FDA under ANADA # 200-704

Manufactured for:

Aspen Veterinary Resource®, LTD., Liberty, MO 64068
pivetalvet.com

Rev. 01/23
Made in India

Neutral Code No. MP/DRUGS/25/90/2020

Information for Dog Owners

CoxibaTM (deracoxib)

Chewable Tablets

For Oral Use in Dogs Only
Do Not Use in Cats

Information for Dog Owners

Coxiba™ (deracoxib) Chewable Tablets are for the control of pain and inflammation due to osteoarthritis or following orthopedic and dental surgery. This summary contains important information about Coxiba Chewable Tablets. You should read this information before starting your dog on Coxiba Chewable Tablets. This sheet is provided only as a summary and does not take the place of instructions from your veterinarian. Talk to your veterinarian if you do not understand any of this information or you want to know more about Coxiba Chewable Tablets.

What is Coxiba Chewable Tablets?
Coxiba Chewable Tablets are a prescription non-steroidal anti-inflammatory drug (NSAID) of the coxib class. They are indicated for the control of postoperative pain and inflammation associated with orthopedic (bone) and dental surgery in dogs and for the control of pain and inflammation (soreness) associated with osteoarthritis in dogs. The tablets are flavored to make administration more convenient.

What kind of results can I expect when my dog takes Coxiba Chewable Tablets for postoperative orthopedic and dental pain and inflammation?

Coxiba Chewable Tablets allow your dog to recover more comfortably by controlling pain and inflammation that follow orthopedic and dental surgery.

• The postoperative orthopedic pain dose is a higher dose; administration at this dose should not exceed 7 days total, including the days the patient is administered Coxiba Chewable Tablets while in the hospital.

• Control of pain and inflammation may vary from dog to dog.

• If Coxiba Chewable Tablets are not given according to your veterinarian's directions, your dog's pain may return.

• Consult your veterinarian if your dog appears to be uncomfortable.

What kind of results can I expect when my dog takes Coxiba Chewable Tablets for pain and inflammation due to osteoarthritis?
Osteoarthritis is a painful condition caused by damage to cartilage and other parts of the joint that may result in the following changes or signs in your dog:
• Limping or lameness
• Decreased activity or exercise (reluctance to stand, climb stairs, jump or run, or difficulty in performing these activities)
• Stiffness or decreased movement of joints
While Coxiba Chewable Tablets is not a cure for osteoarthritis, it can control the pain and inflammation of osteoarthritis and improve your dog's mobility. Response may vary from dog to dog but can be quite dramatic. Coxiba Chewable Tablets may need to be given on a periodic basis for the animal's lifetime. Use the lowest dose to provide adequate relief. Always consult with your veterinarian before altering the dose.

What dogs should not take Coxiba Chewable Tablets?
Your dog should not be given Coxiba Chewable Tablets if s/he:
• Has had an allergic reaction to deracoxib, the active ingredient in Coxiba Chewable Tablets
• Has had an allergic reaction (such as hives, facial swelling, or red or itchy skin) to aspirin or other NSAIDs
• Is presently taking aspirin, other NSAIDs, or corticosteroids (unless directed by your veterinarian)
• Has bloody stool or vomit
• Has a pre-existing kidney or liver condition
• Has any condition predisposing to dehydration
• Is anorexic (loss of appetite)

Coxiba Chewable Tablets should only be given to dogs. Do not use in cats.
People should not take Coxiba Chewable Tablets. Keep Coxiba Chewable Tablets and all medication out of reach of children.
Call your physician immediately if you accidentally take Coxiba Chewable Tablets.

What to discuss with your veterinarian before giving Coxiba Chewable Tablets?
Tell your veterinarian about:
• Any side effects your dog has experienced from Coxiba Chewable Tablets or other NSAIDs
• Any digestive upset (vomiting or diarrhea) your dog has had
• Any kidney disease your dog has had
• Any other medical problems or allergies that your dog has now or has had in the past
• All medications that you are giving your dog or plan to give your dog, including those you can get without prescription and
any dietary supplements
• If you plan to breed your dog, or if your dog is pregnant or nursing
Talk to your veterinarian about:
• The orthopedic or dental surgery your dog will undergo
• What tests might be done before surgery is performed or Coxiba Chewable Tablets are prescribed
• The signs of pain or inflammation that may occur after surgery
• Normal events that can be expected after your dog undergoes surgery
• The proper amount of exercise after surgery to aid recovery
• The signs of osteoarthritis you have observed (for example, limping or stiffness)
• The importance of weight control, physical therapy and exercise in the management of osteoarthritis
• How often your dog may need to be examined by your veterinarian
• The risks and benefits of using Coxiba Chewable Tablets

How to give Coxiba Chewable Tablets to your dog.
Coxiba Chewable Tablets should be given according to your veterinarian's instructions. Your veterinarian will tell you what amount of Coxiba Chewable Tablets is right for your dog and for how long they should be given. Do not change the way you give Coxiba Chewable Tablets to your dog without first speaking with your veterinarian. Coxiba Chewable Tablets should be given by mouth and may be given with or without food, although with food is preferable.

What are the possible side effects that may occur in my dog during therapy with Coxiba Chewable Tablets?
Coxiba Chewable Tablets may cause some side effects in individual dogs. Serious side effects associated with this drug can occur with or without warning and, in some cases, result in death. The most common side effects associated with Coxiba Chewable Tablets therapy involve the digestive tract (vomiting, decreased appetite and diarrhea). Liver and kidney problems have also been reported. It is important to stop the medication and contact your veterinarian immediately if you think your dog may have a medical problem or side effect while on Coxiba Chewable Tablets. If you have additional questions about possible side effects, talk with your veterinarian or call the manufacturer at 1-833-571-1525.
Look for the following side effects that may indicate that your dog is having a problem with Coxiba Chewable Tablets or may
have another medical problem:
• Vomiting
• Decrease in appetite
• Change in behavior, such as depression, restlessness, aggression or apprehension
• Change in bowel movements such as diarrhea or change in stool color (black, tarry or bloody stool)
• Change in drinking or urination
• Yellowing of gums, skin or whites of the eyes (jaundice)

Can Coxiba Chewable Tablets be given with other medications?
Coxiba Chewable Tablets should not be given with other non-steroidal anti-inflammatory drugs (NSAIDs) or corticosteroids (for example, aspirin, carprofen, etodolac, prednisone).
Tell your veterinarian about all medications that you have given your dog in the past, and any medications that you are planning to give with Coxiba Chewable Tablets. This should include any medications that you can get without a prescription and any dietary supplements. Your veterinarian may want to evaluate the potential for any drug interactions and to assure drug compatibility.

What can I do in case my dog eats more than the prescribed amount of Coxiba Chewable Tablets?
Contact your veterinarian immediately if your dog eats more than the prescribed amount of Coxiba Chewable Tablets.

What else should I know about Coxiba Chewable Tablets?
This sheet provides a summary of information about Coxiba Chewable Tablets. If you have any questions or concerns about Coxiba Chewable Tablets, postoperative orthopedic and dental pain and inflammation, or osteoarthritis, talk to your veterinarian.
As with all prescribed medications, Coxiba Chewable Tablets should only be given to the dog for which they are prescribed. They should be given to your dog only for the condition for which they were prescribed, at the prescribed dose, as directed by your veterinarian. It is important to periodically discuss your dog's response to Coxiba Chewable Tablets at regular checkups. Your veterinarian will best determine if your dog is responding as expected and if your dog should continue receiving Coxiba Chewable Tablets.

Keep Coxiba in a secure location out of reach of dogs, cats, and other animals to prevent accidental ingestion or overdose. Use within 90 days of splitting. Approved by FDA under ANADA # 200-704

Manufactured for:

Aspen Veterinary Resource®, LTD., Liberty, MO 64068

pivetalvet.com | P237FPH Rev. 01/23

Made in India Neutral Code No.MP/DRUGS/25/90/2020

PRINCIPAL DISPLAY PANEL - 12 mg x 30 count

NDC: 46066-105-36
COXIBATM
(deracoxib)
CHEWABLE TABLETS
For Oral Use in Dogs Only
Do Not Use in Cats
A coxib-class NSAID
12 mg
Caution: Federal law (U.S.) restricts this drug to use by or on the order of a licensed veterinarian.
Approved by FDA under ANADA #200-704
30 Tablets

PRINCIPAL DISPLAY PANEL - 12 mg x 90 count

NDC: 46066-105-37

COXIBATM (deracoxib)
CHEWABLE TABLETS

For Oral Use in Dogs Only
Do Not Use in Cats
A coxib-class NSAID

12 mg

Caution: Federal law (U.S.) restricts this drug to use by or on the order of a licensed veterinarian.

Approved by FDA under ANADA #200-704

90 Tablets

PRINCIPAL DISPLAY PANEL - 25 mg x 30 count

NDC: 46066-106-36
COXIBATM

(deracoxib)

CHEWABLE TABLETS

For Oral Use in Dogs Only

Do Not Use in Cats
A coxib-class NSAID

25 mg

Caution: Federal law (U.S.) restricts this drug to use by or on the order of a licensed veterinarian.

Approved by FDA under ANADA #200-704

30 Tablets

PRINCIPAL DISPLAY PANEL - 25 mg x 90 count

NDC: 46066-106-37

COXIBATM

(deracoxib) CHEWABLE TABLETS

For Oral Use in Dogs Only
Do Not Use in Cats
A coxib-class NSAID

25 mg

Caution: Federal law (U.S.) restricts this drug to use by or on the order of a licensed veterinarian.

Approved by FDA under ANADA #200-704

90 Tablets

PRINCIPAL DISPLAY PANEL - 75 mg x 30 count

NDC: 46066-107-36
COXIBATM

(deracoxib)
CHEWABLE TABLETS

For Oral Use in Dogs Only
Do Not Use in Cats
A coxib-class NSAID

75 mg

Caution: Federal law (U.S.) restricts this drug to use by or on the order of a licensed veterinarian.

Approved by FDA under ANADA #200-704

30 Tablets

PRINCIPAL DISPLAY PANEL - 75 mg x 90 count

NDC: 46066-107-37

COXIBATM
(deracoxib)
CHEWABLE TABLETS

For Oral Use in Dogs Only

Do Not Use in Cats
A coxib-class NSAID

75 mg

Caution: Federal law (U.S.) restricts this drug to use by or on the order of a licensed veterinarian.

Approved by FDA under ANADA #200-704

90 Tablets

PRINCIPAL DISPLAY PANEL - 100 mg x 30 count

NDC: 46066-104-36
COXIBATM

(deracoxib)
CHEWABLE TABLETS

For Oral Use in Dogs Only
Do Not Use in Cats
A coxib-class NSAID

100 mg

Caution: Federal law (U.S.) restricts this drug to use by or on the order of a licensed veterinarian.

Approved by FDA under ANADA #200-704

30 Tablets

PRINCIPAL DISPLAY PANEL - 100 mg x 90 count

NDC: 46066-104-37

COXIBATM

(deracoxib)
CHEWABLE TABLETS

For Oral Use in Dogs Only
Do Not Use in Cats
A coxib-class NSAID

100 mg

Caution: Federal law (U.S.) restricts this drug to use by or on the order of a licensed veterinarian.

Approved by FDA under ANADA #200-704

90 Tablets